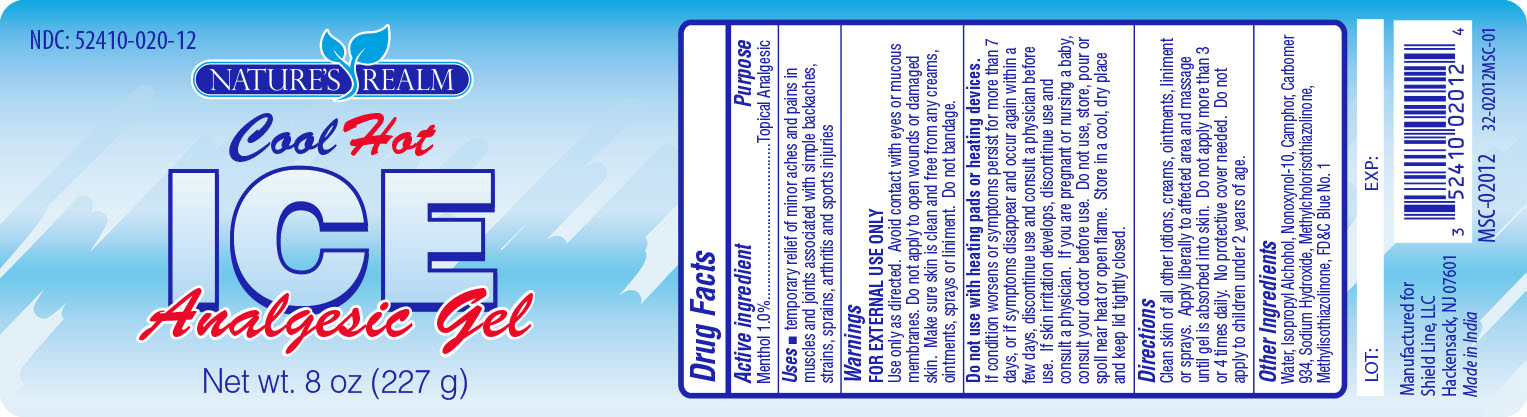 DRUG LABEL: Cool Hot Ice Analgesic Gel
NDC: 52410-0201 | Form: GEL
Manufacturer: SHIELD LINE LLC
Category: otc | Type: HUMAN OTC DRUG LABEL
Date: 20190524

ACTIVE INGREDIENTS: MENTHOL 2.27 g/227 g
INACTIVE INGREDIENTS: ISOPROPYL ALCOHOL; NONOXYNOL-10; CAMPHOR (SYNTHETIC); CARBOMER 934; SODIUM HYDROXIDE; METHYLCHLOROISOTHIAZOLINONE; METHYLISOTHIAZOLINONE; FD&C BLUE NO. 1; WATER

Active Ingredient

Menthol 1.0%

Purpose

Topical Analgesic

Uses:

- temporary relief of minor aches and pains in muscles and joints associated with simple backaches, strains, sprains, arthritis and sports injuries

Warnings

FOR EXTERNAL USE ONLY

Use only as directed. Avoid contact with eyes or mucous membranes. Do not apply to open wounds or damaged skin. Make sure skin is clean and free from any creams , ointments , sprays or liniment. Do not bandage.

Do not use with heating pads or heating devices

If condition worsens or symptoms persist for more than 7 days, or if symptoms disappear and occur again within a few days, discontinue use and consult a physician before use. If skin irritation develops, discontinue use and consult a physician. If you are pregnant or nursing a baby, consult your doctor before use. Do not use, store, pour or spoll near heat or open flame. Store in a cool, dry place and keep lid tightly closed.

KEEP OUT OF REACH OF CHILDREN

In case of accidental ingestion, get medical help or contact a Poison Control Center right away

Directions

Clean skin of all other lotions, creams, ointments, liniment, or sprays. Apply liberally to affected area and massage until gel is absorbed into skin. Do not apply more than 3 or 4 times daily. No protective cover needed. Do not apply to children under 2 years or age.

Inactive Ingredients

Water, Isopropyl Alchohol , Nonoxynol-10, Camphor, Carbomer 934, Sodium Hydroxide, Methylchloroisothiazolinone & Methylisothiazolinone, FD&C Blue no. 1